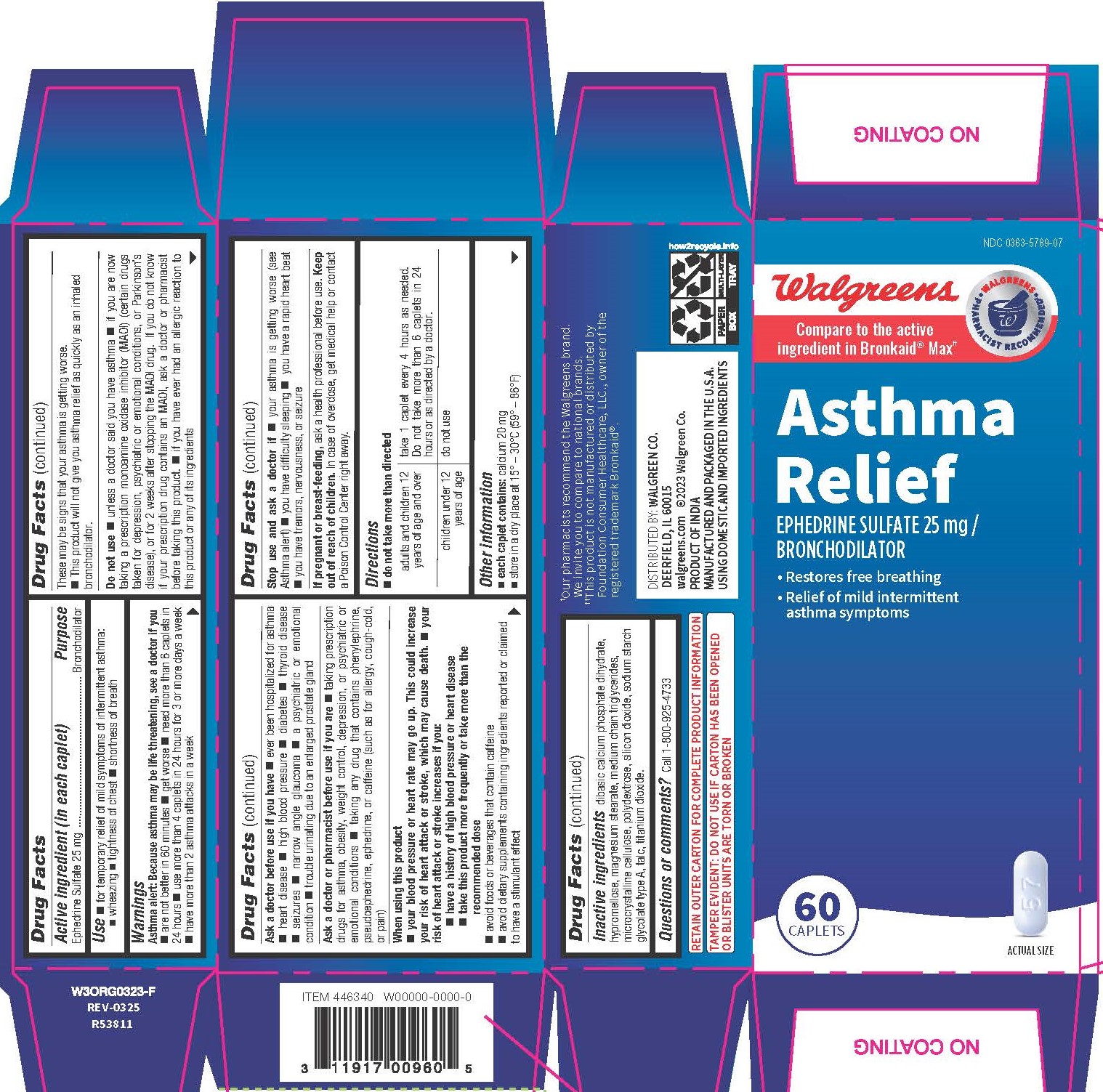 DRUG LABEL: Ephedrine Sulfate
NDC: 0363-5789 | Form: TABLET, FILM COATED
Manufacturer: Walgreen Company
Category: otc | Type: HUMAN OTC DRUG LABEL
Date: 20250904

ACTIVE INGREDIENTS: EPHEDRINE SULFATE 25 mg/1 1
INACTIVE INGREDIENTS: SILICON DIOXIDE; MICROCRYSTALLINE CELLULOSE; POLYDEXTROSE; CALCIUM PHOSPHATE, DIBASIC, DIHYDRATE; TITANIUM DIOXIDE; MAGNESIUM STEARATE; SODIUM STARCH GLYCOLATE TYPE A POTATO; HYPROMELLOSES; TALC; MEDIUM-CHAIN TRIGLYCERIDES

5789 - Walgreen

Drug Facts

Active ingredient (in each caplet)
Ephedrine Sulfate 25 mg

Purpose
Bronchodilator

Use

 for temporary relief of mild symptoms of intermittent asthma:
 wheezing  tightness of chest  shortness of breath

WARNINGS

Asthma alert: Because asthma may be life threatening, see a doctor if you
 are not better in 60 minutes

 get worse

 need more than 6 caplets in 24 hours

 use more than 4 caplets in 24 hours for 3 or more days a week
 have more than 2 asthma attacks in a week

These may be signs that your asthma is getting worse.
 This product will not give you asthma relief as quickly as an inhaled bronchodilator.

Do not use

 unless a doctor said you have asthma

 if you are now taking a prescription monoamine oxidase inhibitor (MAOI) (certain drugs taken for depression, psychiatric or emotional conditions, or Parkinson’s disease), or for 2 weeks after stopping the MAOI drug. If you do not know if your prescription drug contains an MAOI, ask a doctor or pharmacist before taking this product.

 if you have ever had an allergic reaction to this product or any of its ingredients

Ask a doctor before use if you have

 ever been hospitalized for asthma
 heart disease

 high blood pressure

 diabetes

 thyroid disease
 seizures

 narrow angle glaucoma

 a psychiatric or emotional condition

 trouble urinating due to an enlarged prostate gland

Ask a doctor or pharmacist before use if you are

 taking prescription drugs for asthma, obesity, weight control, depression, or psychiatric or emotional conditions

 taking any drug that contains phenylephrine, pseudoephedrine, ephedrine, or caffeine (such as for allergy, cough-cold, or pain)

When using this product
 your blood pressure or heart rate may go up. This could increase your risk of heart attack or stroke, which may cause death.

 your risk of heart attack or stroke increases if you:
 have a history of high blood pressure or heart disease
 take this product more frequently or take more than the recommended dose
 avoid foods or beverages that contain caffeine
 avoid dietary supplements containing ingredients reported or claimed to have a stimulant effect

Stop use and ask a doctor if

 your asthma is getting worse (see Asthma alert)

 you have difficulty sleeping

 you have a rapid heart beat
 you have tremors, nervousness, or seizure

PREGNANCY OR BREAST FEEDING

If pregnant or breast-feeding, ask a health professional before use.

Keep out of reach of children.

OVERDOSAGE

In case of overdose, get medical help or contact a Poison Control Center right away.

Directions

 do not take more than directed

adults and children 12 years of age and over | take 1 caplet every 4 hours as needed. Do not take more than 6 caplets in 24 hours or as directed by a doctor.
children under 12 years of age | do not use

Other information

- each caplet contains: calcium 20 mg
- store in a dry place at 15° – 30°C (59° – 86°F)

INACTIVE INGREDIENT

dibasic calcium phosphate dihydrate, hypromellose, magnesium stearate, medium chain triglycerides, microcrystalline cellulose, polydextrose, silicon dioxide, sodium starch glycolate type A, talc, titanium dioxide.

Questions or comments?

Call 1-800-925-4733

RETAIN OUTER CARTON FOR COMPLETE PRODUCT INFORMATION

TAMPER EVIDENT: DO NOT USE IF CARTON HAS BEEN OPENED OR BLISTER UNITS ARE TORN OR BROKEN

DISTRIBUTED BY: WALGREEN CO.
DEERFIELD, IL 60015
walgreens.com ©2023 Walgreen Co.
PRODUCT OF INDIA MANUFACTURED AND PACKAGED IN THE U.S.A. USING DOMESTIC AND IMPORTED INGREDIENTS

††This product is not manufactured or distributed by Foundation Consumer Healthcare, LLC., owner of the registered trademark Bronkaid®.

PACKAGE LABEL

NDC 0363-5789-07

Walgreens

Compare to the active ingredient in Bronkaid® Max††

Asthma Relief

Ephedrine Sulfate 25 mg/ Bronchodilator

• Restores free breathing • Relief of mild intermittent asthma symptoms

60 Caplets